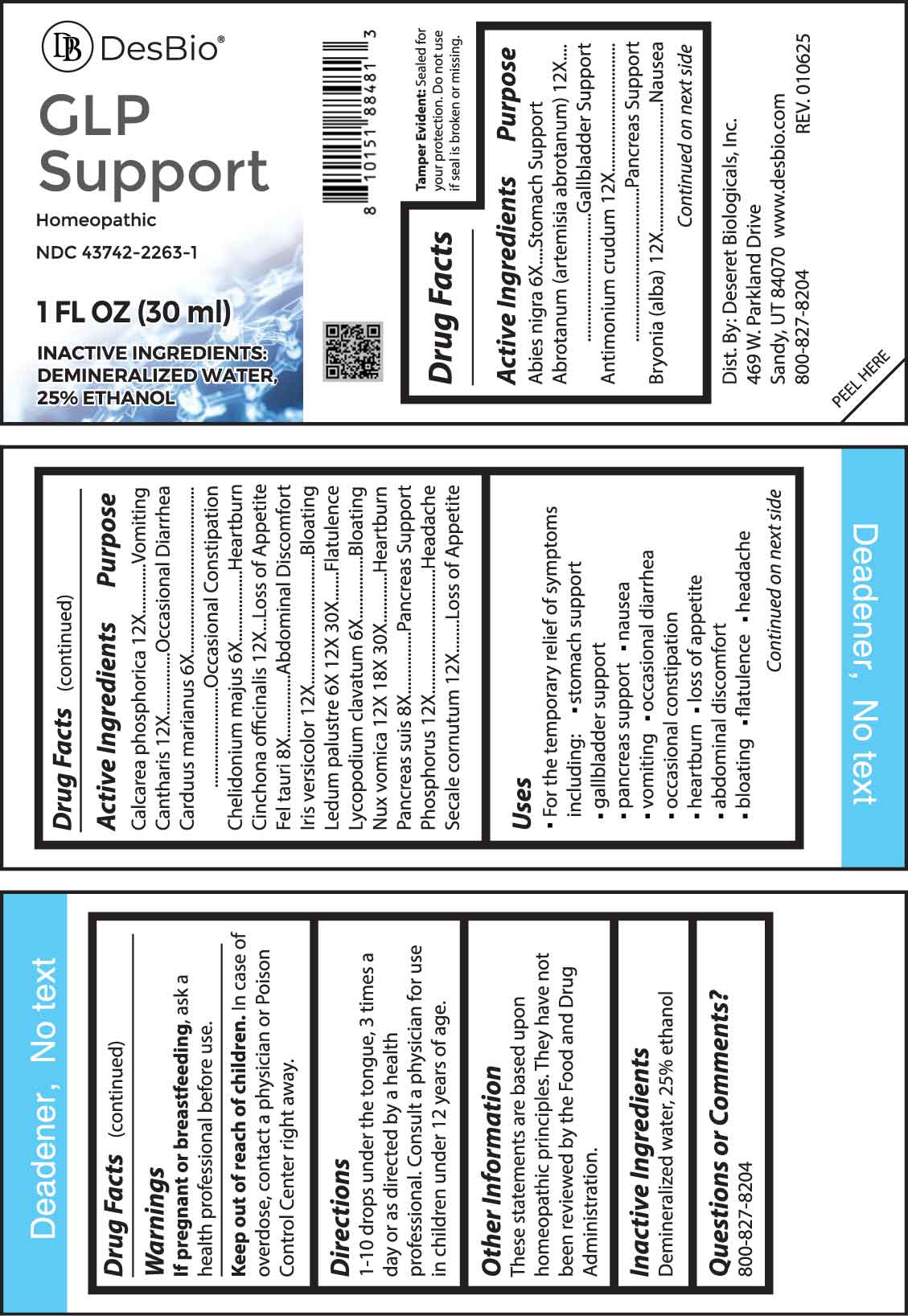 DRUG LABEL: GLP Support
NDC: 43742-2263 | Form: LIQUID
Manufacturer: Deseret Biologicals, Inc.
Category: homeopathic | Type: HUMAN OTC DRUG LABEL
Date: 20250507

ACTIVE INGREDIENTS: PICEA MARIANA RESIN 6 [hp_X]/1 mL; ARTEMISIA ABROTANUM FLOWERING TOP 12 [hp_X]/1 mL; ANTIMONY TRISULFIDE 12 [hp_X]/1 mL; BRYONIA ALBA ROOT 12 [hp_X]/1 mL; TRIBASIC CALCIUM PHOSPHATE 12 [hp_X]/1 mL; LYTTA VESICATORIA 12 [hp_X]/1 mL; MILK THISTLE 6 [hp_X]/1 mL; CHELIDONIUM MAJUS WHOLE 6 [hp_X]/1 mL; CINCHONA OFFICINALIS BARK 12 [hp_X]/1 mL; BOS TAURUS BILE 8 [hp_X]/1 mL; IRIS VERSICOLOR ROOT 12 [hp_X]/1 mL; RHODODENDRON TOMENTOSUM LEAFY TWIG 6 [hp_X]/1 mL; LYCOPODIUM CLAVATUM SPORE 6 [hp_X]/1 mL; STRYCHNOS NUX-VOMICA SEED 12 [hp_X]/1 mL; SUS SCROFA PANCREAS 8 [hp_X]/1 mL; PHOSPHORUS 12 [hp_X]/1 mL; CLAVICEPS PURPUREA SCLEROTIUM 12 [hp_X]/1 mL
INACTIVE INGREDIENTS: WATER; ALCOHOL

DRUG FACTS:

ACTIVE INGREDIENTS:

Abies Nigra 6X, Abrotanum (Artemisia Abrotanum) 12X, Antimonium Crudum 12X, Bryonia (Alba) 12X, Calcarea Phosphorica 12X, Cantharis 12X, Carduus Marianus 6X, Chelidonium Majus 6X, Cinchona Officinalis 12X, Fel Tauri 8X, Iris Versicolor 12X, Ledum Palustre 6X, 12X, 30X, Lycopodium Clavatum 6X, Nux Vomica 12X, 18X, 30X, Pancreas Suis 8X, Phosphorus 12X, Secale Cornutum 12X.

PURPOSE:

Abies Nigra – Stomach Support, Abrotanum (Artemisia Abrotanum) – Gallbladder Support, Antimonium Crudum – Pancreas Support, Bryonia (Alba) - Nausea, Calcarea Phosphorica - Vomiting, Cantharis – Occasional Diarrhea, Carduus Marianus – Occasional Constipation, Chelidonium Majus - Heartburn, Cinchona Officinalis – Loss of Appetite, Fel Tauri – Abdominal Discomfort, Iris Versicolor - Bloating, Ledum Palustre - Flatulence, Lycopodium Clavatum - Bloating, Nux Vomica - Heartburn, Pancreas Suis – Pancreas Support, Phosphorus - Headache, Secale Cornutum – Loss of Appetite

USES:

• For the temporary relief of symptoms including:
• stomach support • gallbladder support • pancreas support • nausea • vomiting

• occasional diarrhea • occasional constipation• heartburn • loss of appetite

• abdominal discomfort • bloating • flatulence • headache

These statements are based upon homeopathic principles. They have not been reviewed by the Food and Drug Administration.

WARNINGS:

If pregnant or breastfeeding, ask a health professional before use.

Keep out of reach of children. In case of overdose, contact a physician or Poison Control Center right away.

Tamper Evident: Sealed for your protection. Do not use if seal is broken or missing.

KEEP OUT OF REACH OF CHILDREN:

In case of overdose, contact a physician or Poison Control Center right away.

DIRECTIONS:

1-10 drops under the tongue, 3 times a day or as directed by a health professional. Consult a physician for use in children under 12 years of age.

INACTIVE INGREDIENTS:

Demineralized water, 25% ethanol

QUESTIONS:

Dist. By: Deseret Biologicals, Inc.

469 W. Parkland Drive

Sandy, UT 84070

www.desbio.co

800-827-8204

PACKAGE LABEL DISPLAY:

DesBio

GLP Support

Homeopathic

NDC 43742-2263-1

1 FL OZ (30 ml)